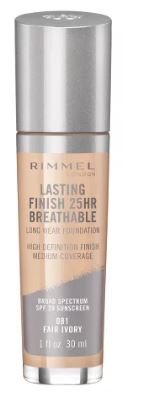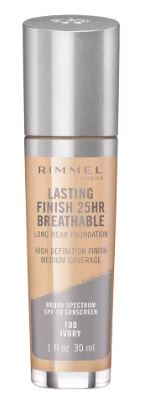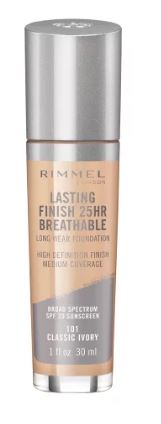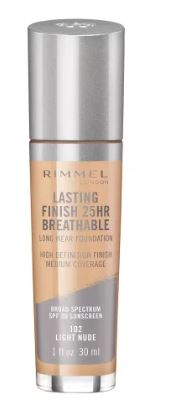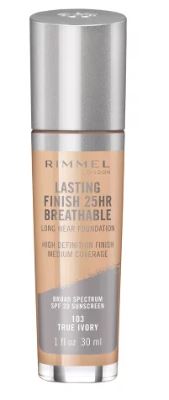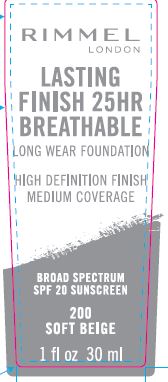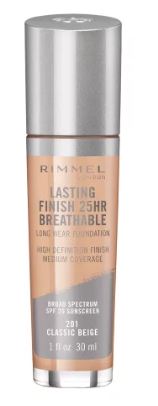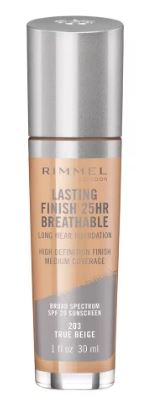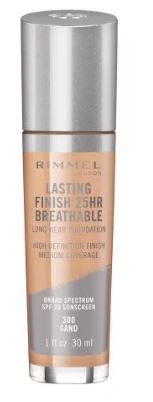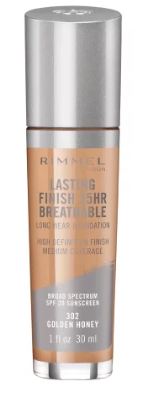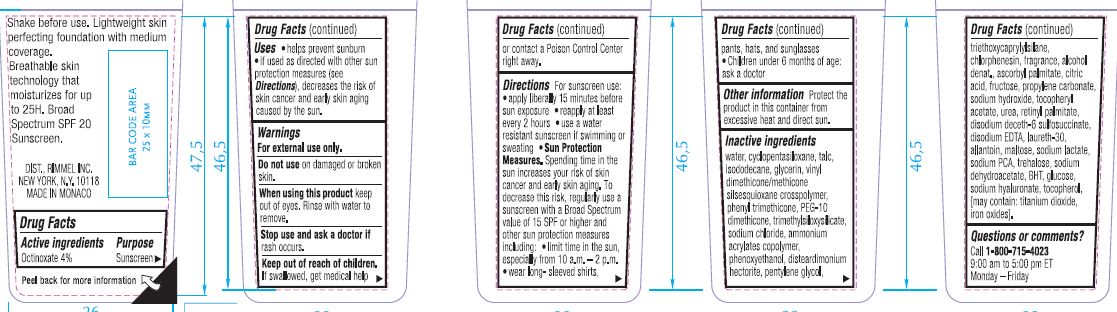 DRUG LABEL: Rimmel Lasting Breathable Foundation SPF 20
NDC: 76485-1111 | Form: LIQUID
Manufacturer: Rimmel Inc.
Category: otc | Type: HUMAN OTC DRUG LABEL
Date: 20200210

ACTIVE INGREDIENTS: OCTINOXATE 4 g/100 mL
INACTIVE INGREDIENTS: ISODODECANE; GLYCERIN; DISTEARDIMONIUM HECTORITE; TALC; PEG-10 DIMETHICONE (600 CST); SODIUM CHLORIDE; PHENOXYETHANOL; CHLORPHENESIN; ASCORBYL PALMITATE; SODIUM HYDROXIDE; SODIUM LACTATE; PROPYLENE CARBONATE; TRIMETHYLSILOXYSILICATE (M/Q 0.6-0.8); SODIUM DEHYDROACETATE; TRIETHOXYCAPRYLYLSILANE; WATER; PHENYL TRIMETHICONE; PENTYLENE GLYCOL; ALLANTOIN

Rimmel Lasting Finish Breathable Foundation SPF 20

Active ingredients

Octinoxate 4%

Purpose

Sunscreen

Uses

- helps prevent sunburn
- if used as directed with other sun protection measures (see Directions), decreases the risk of skin cancer and early skin aging caused by the sun.

Warnings

For external use only.

Do not use

on damaged or broken skin.

When using this product

keep out of eyes. Rinse with water to remove.

Stop use and ask a doctor

if rash occurs.

Keep out of reach of children.

If swallowed, get medical help or contact a Poison Control Center right away.

Directions

For sunscreen use:

- apply liberally 15 minutes before sun exposure
- reapply at least every 2 hours
- use a water resistant sunscreen if swimming or sweating
- Sun Protection Measures. Spending time in the sun increases your risk of skin cancer and early skin aging. To decrease this risk, regularly use a sunscreen with a Broad Spectrum SPF value of 15 or higher and other sun protection measures including: [bullet] limit time in the sun, especially from 10 a.m.-2 p.m. [bullet] wear long-sleeved shirts, pants, hats, and sunglasses.
- Children under 6 months of age: ask a doctor

Other information

Protect the product in this container from excessive heat and direct sun.

Inactive ingredients

WATER, CYCLOPENTASILOXANE, TALC, ISODODECANE, GLYCERIN, VINYL DIMETHICONE/METHICONE SILSESQUIOXANE CROSSPOLYMER, PHENYL TRIMETHICONE, PEG-10 DIMETHICONE, TRIMETHYLSILOXYSILICATE, SODIUM CHLORIDE, AMMONIUM ACRYLATES COPOLYMER, PHENOXYETHANOL, DISTEARDIMONIUM HECTORITE, PENTYLENE GLYCOL, TRIETHOXYCAPRYLYLSILANE, CHLORPHENESIN, FRAGRANCE, ALCOHOL DENAT., ASCORBYL PALMITATE, CITRIC ACID, FRUCTOSE, PROPYLENE CARBONATE, SODIUM HYDROXIDE, TOCOPHERYL ACETATE, UREA, RETINYL PALMITATE, DISODIUM DECETH-6 SULFOSUCCINATE, DISODIUM EDTA, LAURETH-30, ALLANTOIN, MALTOSE, SODIUM LACTATE, SODIUM PCA, TREHALOSE, SODIUM DEHYDROACETATE, BHT, GLUCOSE, SODIUM HYALURONATE, TOCOPHEROL, [May Contain: TITANIUM DIOXIDE, IRON OXIDES]

Questions or comments?

Call 1-800-715-4023

9:00 am to 5:00 pm ET

Monday - Friday

PACKAGE LABEL

RIMMEL

LONDON

LASTING

FINISH 25 HR

BREATHABLE

LONG WEAR FOUNDATION

HIGH DEFINITION FINISH

MEDIUM COVERAGE

BROAD SPECTRUM

SPF 20 SUNSCREEN

1 fl oz 30 ml